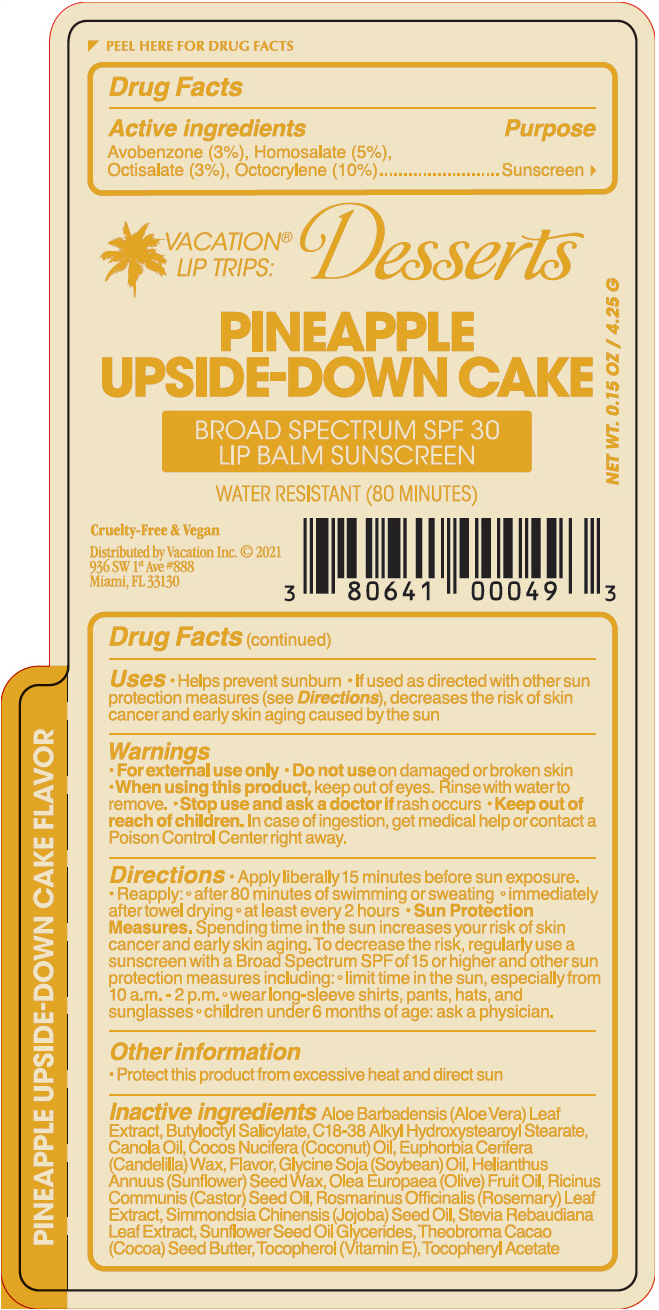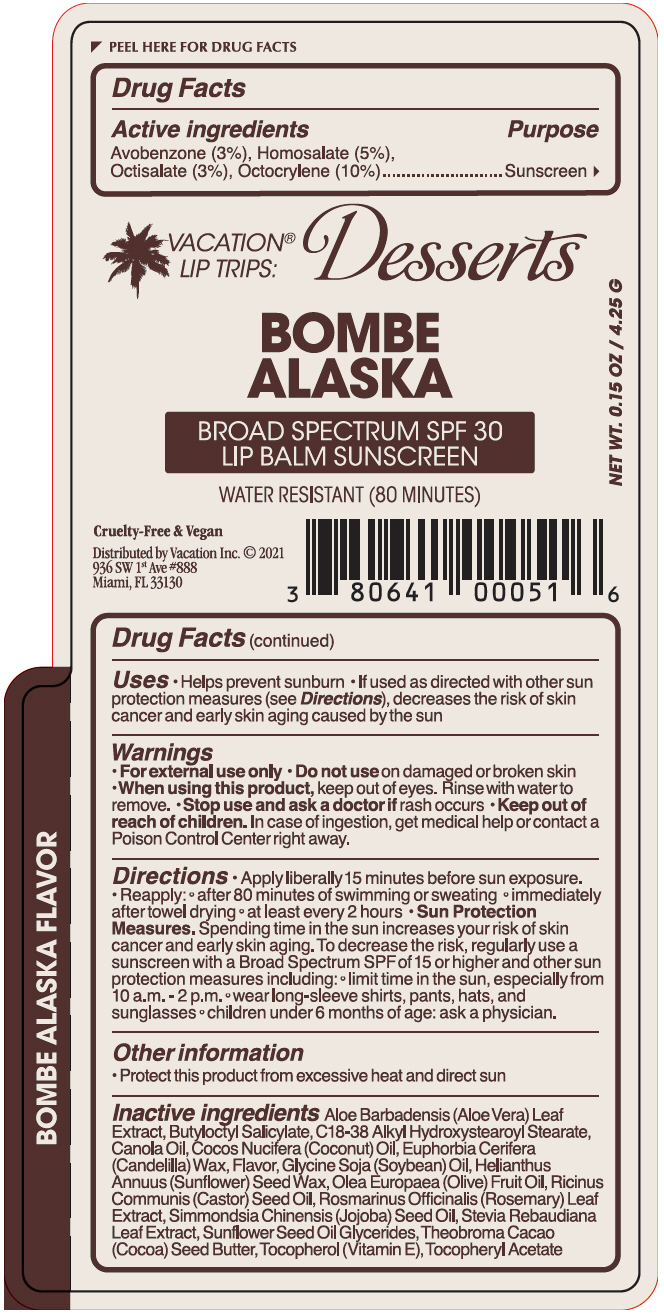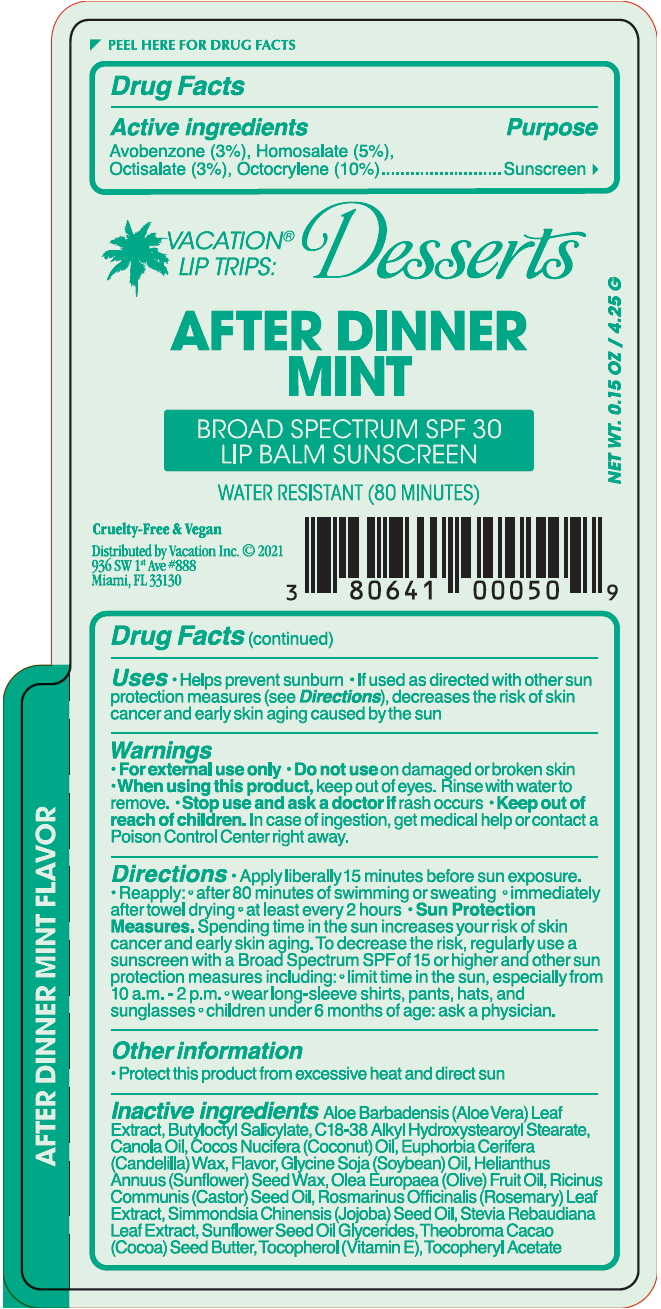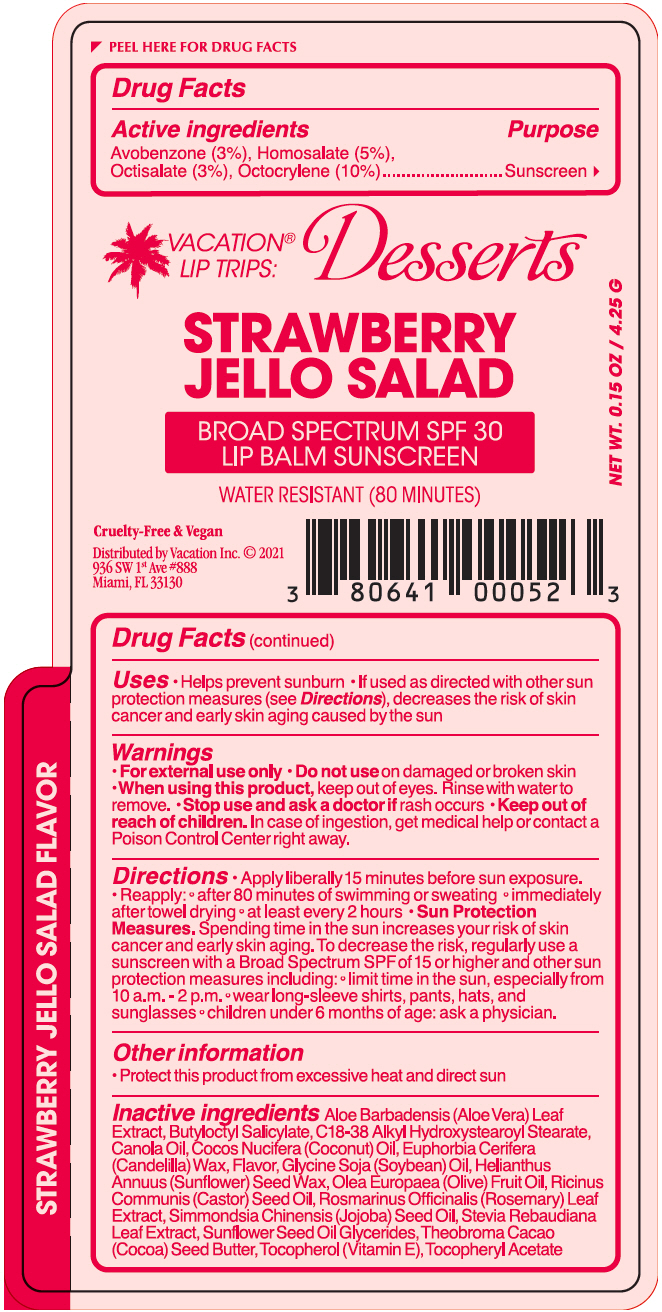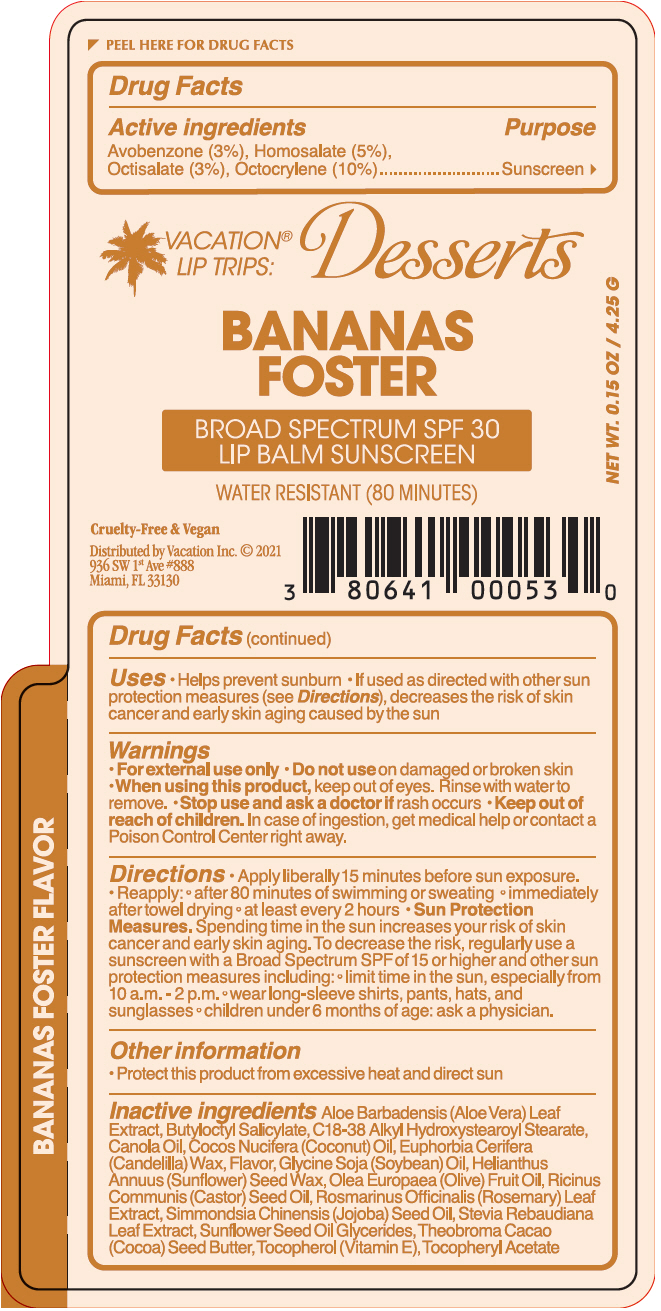 DRUG LABEL: Vacation Lip Trips Desserts 
NDC: 80641-100 | Form: STICK
Manufacturer: Vacation Inc.
Category: otc | Type: HUMAN OTC DRUG LABEL
Date: 20220105

ACTIVE INGREDIENTS: Avobenzone 0.03 g/1 g; Homosalate 0.05 g/1 g; Octisalate 0.03 g/1 g; Octocrylene 0.1 g/1 g
INACTIVE INGREDIENTS: Aloe Vera Leaf; Butyloctyl Salicylate; C18-38 Alkyl Hydroxystearoyl Stearate; Canola Oil; Coconut Oil; Candelilla Wax; Soybean Oil; Helianthus Annuus Seed Wax; Olive Oil; Castor Oil; Rosemary; Jojoba Oil; Stevia Rebaudiuna Leaf; Cocoa Butter; .Alpha.-Tocopherol; .Alpha.-Tocopherol Acetate

Vacation® Lip Trips Desserts

Drug Facts

Active ingredients

Avobenzone (3%), Homosalate (5%), Octisalate (3%), Octocrylene (10%)

Purpose

Sunscreen

Uses

- Helps prevent sunburn
- If used as directed with other sun protection measures (see Directions), decreases the risk of skin cancer and early skin aging caused by the sun

Warnings

For external use only

- Do not use on damaged or broken skin
- When using this product, keep out of eyes. Rinse with water to remove.
- Stop use and ask a doctor if rash occurs

- Keep out of reach of children. In case of ingestion, get medical help or contact a Poison Control Center right away.

Directions

- Apply liberally 15 minutes before sun exposure.
- Reapply: after 80 minutes of swimming or sweating immediately after towel drying at least every 2 hours
- Sun Protection Measures. Spending time in the sun increases your risk of skin cancer and early skin aging. To decrease the risk, regularly use a sunscreen with a Broad Spectrum SPF of 15 or higher and other sun protection measures including: limit time in the sun, especially from 10 a.m. - 2 p.m. wear long-sleeve shirts, pants, hats, and sunglasses children under 6 months of age: ask a physician.

Other information

- Protect this product from excessive heat and direct sun

Inactive ingredients

Aloe Barbadensis (Aloe Vera) Leaf Extract, Butyloctyl Salicylate, C18-38 Alkyl Hydroxystearoyl Stearate, Canola Oil, Cocos Nucifera (Coconut) Oil, Euphorbia Cerifera (Candelilla) Wax, Flavor, Glycine Soja (Soybean) Oil, Helianthus Annuus (Sunflower) Seed Wax, Olea Europaea (Olive) Fruit Oil, Ricinus Communis (Castor) Seed Oil, Rosmarinus Officinalis (Rosemary) Leaf Extract, Simmondsia Chinensis (Jojoba) Seed Oil, Stevia Rebaudiana Leaf Extract, Sunflower Seed Oil Glycerides, Theobroma Cacao (Cocoa) Seed Butter, Tocopherol (Vitamin E), Tocopheryl Acetate

Distributed by Vacation Inc.
936 SW 1st Ave #888
Miami, FL 33130

PRINCIPAL DISPLAY PANEL - 4.25 G Tube Label - PINEAPPLE UPSIDE-DOWN CAKE

VACATION®
LIP TRIPS:
Desserts

PINEAPPLE
UPSIDE-DOWN CAKE

BROAD SPECTRUM SPF 30
LIP BALM SUNSCREEN

WATER RESISTANT (80 MINUTES)

Cruelty-Free & Vegan

Distributed by Vacation Inc. © 2021
936 SW 1st Ave #888
Miami, FL 33130

NET WT. 0.15 OZ / 4.25 G

PRINCIPAL DISPLAY PANEL - 4.25 G Tube Label - BOMBE ALASKA

VACATION®
LIP TRIPS:
Desserts

BOMBE
ALASKA

BROAD SPECTRUM SPF 30
LIP BALM SUNSCREEN

WATER RESISTANT (80 MINUTES)

Cruelty-Free & Vegan

Distributed by Vacation Inc. © 2021
936 SW 1st Ave #888
Miami, FL 33130

NET WT. 0.15 OZ / 4.25 G

PRINCIPAL DISPLAY PANEL - 4.25 G Tube Label - AFTER DINNER MINT

VACATION®
LIP TRIPS:
Desserts

AFTER DINNER
MINT

BROAD SPECTRUM SPF 30
LIP BALM SUNSCREEN

WATER RESISTANT (80 MINUTES)

Cruelty-Free & Vegan

Distributed by Vacation Inc. © 2021
936 SW 1st Ave #888
Miami, FL 33130

NET WT. 0.15 OZ / 4.25 G

PRINCIPAL DISPLAY PANEL - 4.25 G Tube Label - STRAWBERRY JELLO SALAD

VACATION®
LIP TRIPS:
Desserts

STRAWBERRY
JELLO SALAD

BROAD SPECTRUM SPF 30
LIP BALM SUNSCREEN

WATER RESISTANT (80 MINUTES)

Cruelty-Free & Vegan

Distributed by Vacation Inc. © 2021
936 SW 1st Ave #888
Miami, FL 33130

NET WT. 0.15 OZ / 4.25 G

PRINCIPAL DISPLAY PANEL - 4.25 G Tube Label - BANANAS FOSTER

VACATION®
LIP TRIPS:
Desserts

BANANAS
FOSTER

BROAD SPECTRUM SPF 30
LIP BALM SUNSCREEN

WATER RESISTANT (80 MINUTES)

Cruelty-Free & Vegan

Distributed by Vacation Inc. © 2021
936 SW 1st Ave #888
Miami, FL 33130

NET WT. 0.15 OZ / 4.25 G